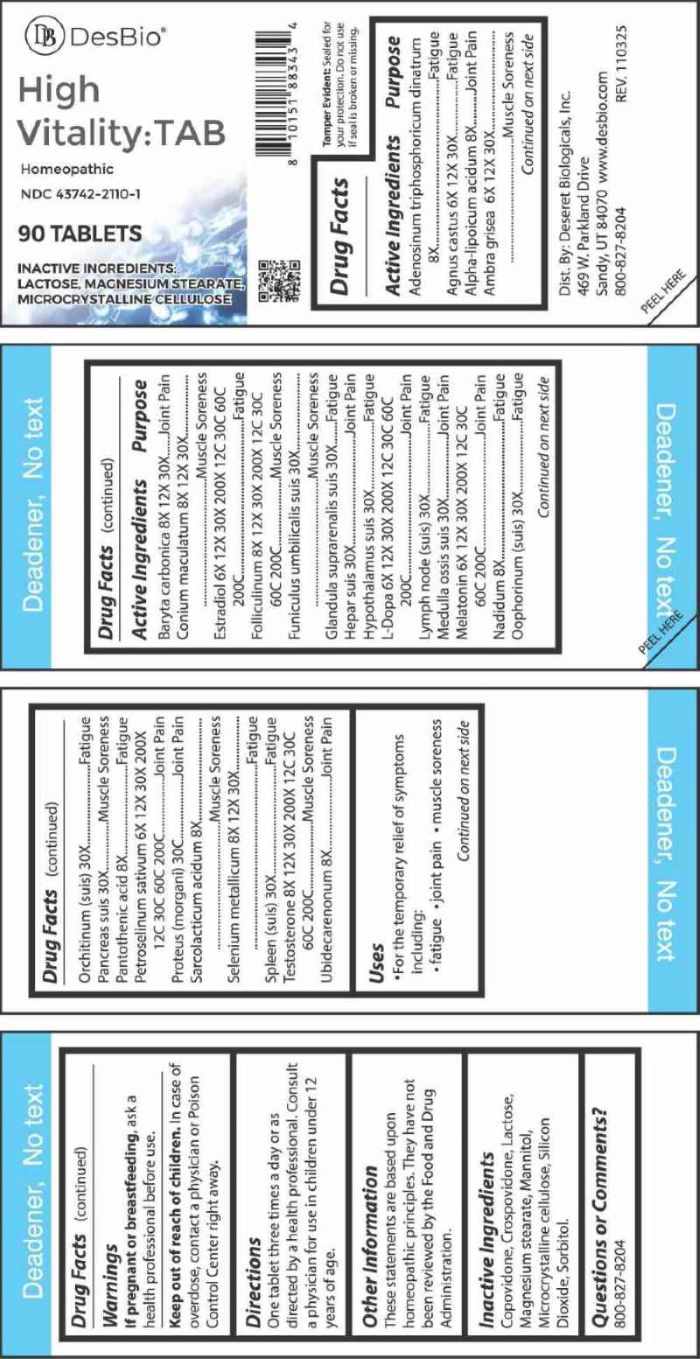 DRUG LABEL: High Vitality Tab
NDC: 43742-2110 | Form: TABLET
Manufacturer: Deseret Biologicals
Category: homeopathic | Type: HUMAN OTC DRUG LABEL
Date: 20251211
DEA Schedule: CIII

ACTIVE INGREDIENTS: CHASTE TREE FRUIT 6 [hp_X]/1 1; AMBERGRIS 6 [hp_X]/1 1; ESTRADIOL 6 [hp_X]/1 1; LEVODOPA 6 [hp_X]/1 1; MELATONIN 6 [hp_X]/1 1; PETROSELINUM CRISPUM WHOLE 6 [hp_X]/1 1; ADENOSINE TRIPHOSPHATE DISODIUM 8 [hp_X]/1 1; ALPHA LIPOIC ACID 8 [hp_X]/1 1; NADIDE 8 [hp_X]/1 1; PANTOTHENIC ACID 8 [hp_X]/1 1; LACTIC ACID, L- 8 [hp_X]/1 1; UBIDECARENONE 8 [hp_X]/1 1; BARIUM CARBONATE 8 [hp_X]/1 1; CONIUM MACULATUM FLOWERING TOP 8 [hp_X]/1 1; SELENIUM 8 [hp_X]/1 1; ESTRONE 8 [hp_X]/1 1; TESTOSTERONE 8 [hp_X]/1 1; SUS SCROFA UMBILICAL CORD 30 [hp_X]/1 1; SUS SCROFA ADRENAL GLAND 30 [hp_X]/1 1; PORK LIVER 30 [hp_X]/1 1; SUS SCROFA HYPOTHALAMUS 30 [hp_X]/1 1; SUS SCROFA LYMPH 30 [hp_X]/1 1; SUS SCROFA BONE MARROW 30 [hp_X]/1 1; SUS SCROFA OVARY 30 [hp_X]/1 1; SUS SCROFA TESTICLE 30 [hp_X]/1 1; SUS SCROFA PANCREAS 30 [hp_X]/1 1; SUS SCROFA SPLEEN 30 [hp_X]/1 1; PROTEUS MORGANII 30 [hp_C]/1 1
INACTIVE INGREDIENTS: LACTOSE MONOHYDRATE; MAGNESIUM STEARATE; CELLULOSE, MICROCRYSTALLINE; COPOVIDONE K25-31; CROSPOVIDONE, UNSPECIFIED; MANNITOL; SILICON DIOXIDE; SORBITOL

DRUG FACTS:

ACTIVE INGREDIENTS:

Adenosinum Triphosphoricum Disodium 8X, Agnus Castus 6X, 12X, 30X, Alpha-Lipoicum Acidum 8X, Ambra Grisea 6X, 12X, 30X, Baryta Carbonica 8X, 12X, 30X, Conium Maculatum 8X, 12X, 30X, Estradiol 6X, 12X, 30X, 200X, 12C, 30C, 60C, 200C, Folliculinum 8X, 12X, 30X, 200X, 12C, 30C, 60C, 200C, Funiculus Umbilicalis Suis 30X, Glandula Suprarenalis Suis 30X, Hepar Suis 30X, Hypothalamus (Suis) 30X, L-Dopa 6X, 12X, 30X, 200X, 12C, 30C, 60C, 200C, Lymph Node (Suis) 30X, Medulla Ossis Suis 30X, Melatonin 6X, 12X, 30X, 200X, 12C, 30C, 60C, 200C, Nadidum 8X, Oophorinum (Suis) 30X, Orchitinum (Suis) 30X, Pancreas Suis 30X, Pantothenic Acid 8X, Petroselinum Sativum 6X, 12X, 30X, 200X, 12C, 30C, 60C, 200C, Proteus (Morgani) 30C, Sarcolacticum Acidum 8X, Selenium Metallicum 8X, 12X, 30X, Spleen (Suis) 30X, Testosterone 8X, 12X, 30X, 200X, 12C, 30C, 60C, 200C, Ubidecarenonum 8X.

PURPOSE:

Adenosinum Triphosphoricum Disodium - Fatigue, Agnus Castus - Fatigue, Alpha-Lipoicum Acidum – Joint Pain, Ambra Grisea – Muscle Soreness, Baryta Carbonica – Joint Pain, Conium Maculatum – Muscle Soreness, Estradiol - Fatigue, Folliculinum – Muscle Soreness, Funiculus Umbilicalis Suis – Muscle Soreness, Glandula Suprarenalis Suis - Fatigue, Hepar Suis – Joint Pain, Hypothalamus Suis - Fatigue, L-Dopa – Joint Pain, Lymph Node (Suis) - Fatigue, Medulla Ossis Suis – Joint Pain, Melatonin – Joint Pain, Nadidum - Fatigue, Oophorinum (Suis) - Fatigue, Orchitinum (Suis) - Fatigue, Pancreas Suis – Muscle Soreness, Pantothenic Acid - Fatigue, Petroselinum Sativum – Joint Pain, Proteus (Morgani) – Joint Pain, Sarcolacticum Acidum – Muscle Soreness, Selenium Metallicum - Fatigue, Spleen (Suis) - Fatigue, Testosterone – Muscle Soreness, Ubidecarenonum – Joint Pain

USES:

• For the temporary relief of symptoms including:

• fatigue • joint pain • muscle soreness
**These statements are based upon homeopathic principles. They have not been reviewed by the Food and Drug Administration.

WARNINGS:

If pregnant or breastfeeding, ask a health professional before use.

Keep out of reach of children. In case of overdose, contact a physicianor Poison Control Center right away.

Tamper Evident: Sealed for your protection. Do not use if seal is broken or missing.

KEEP OUT OF REACH OF CHILDREN:

In case of overdose, contact a physician or Poison Control Center right away.

DIRECTIONS:

One tablet three times a day or as directed by a health professional.

Consult a physician for use in children under 12 years of age.

INACTIVE INGREDIENTS:

Copovidone, Crospovidone, Lactose, Magnesium Stearate, Mannitol, Microcrystalline Cellulose, Silicon Dioxide, Sorbitol

QUESTIONS:

Dist. By: Deseret Biologicals, Inc.

469 W. Parkland Drive

Sandy, UT 84070

www.desbio.com

800-827-8204

PACKAGE LABEL DISPLAY:

DesBio

High Vitality:TAB

Homeopathic

NDC 43742-2110-1

90 TABLETS